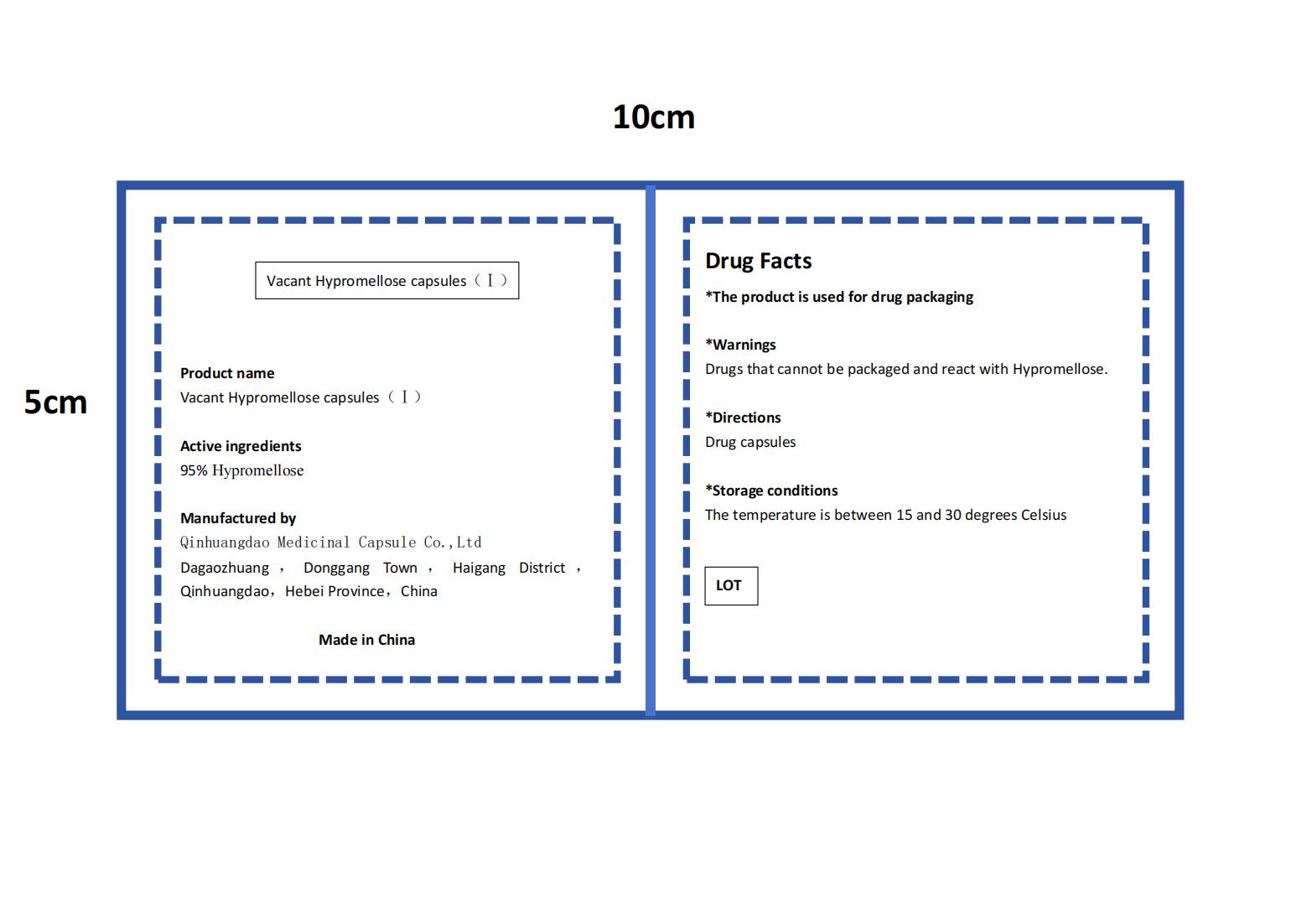 DRUG LABEL: Vacant Hypromellose
NDC: 84175-003 | Form: CAPSULE
Manufacturer: Qinhuangdao Medicinal Capsule Co.,Ltd
Category: otc | Type: HUMAN OTC DRUG LABEL
Date: 20240318

ACTIVE INGREDIENTS: HYPROMELLOSES 0.95 g/1 g
INACTIVE INGREDIENTS: .KAPPA.-CARRAGEENAN 0.05 g/1 g

ACTIVE INGREDIENT

Hypromellose

PURPOSE

Drug capsules

INDICATIONS AND USAGE

Packaging drugs

WARNINGS

Drugs that cannot be packaged and react with Hypromellose

DO NOT USE

Disabled for individuals allergic to Hypermelose

WHEN USING

Take the capsule orally

STOP USE

Discomfort occurs, please stop using and seek medical attention immediately

KEEP OUT OF REACH OF CHILDREN

Please keep the product out of reach of children

STORAGE AND HANDLING

The temperature is between 15 and 30 degrees Celsius

INACTIVE INGREDIENT

Kappa Carrageenan

DOSAGE AND ADMINISTRATION

Each capsule contains only one medication